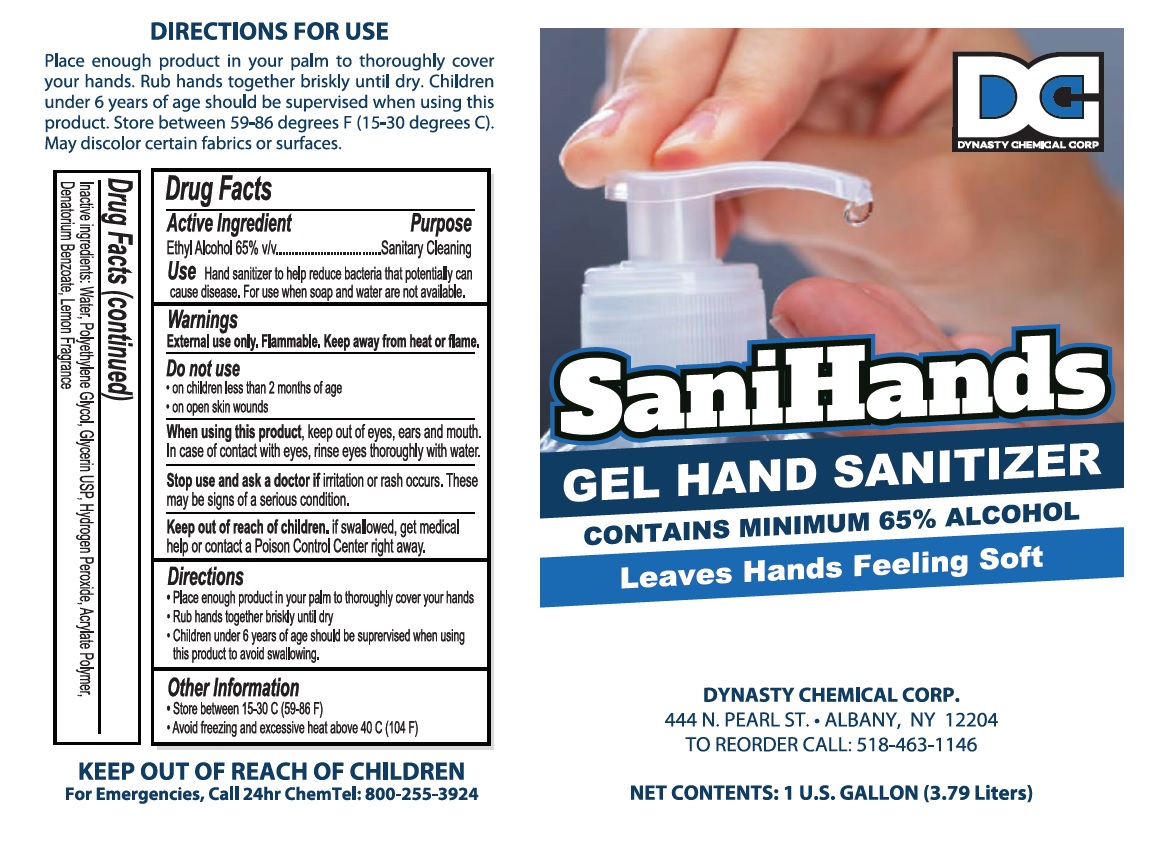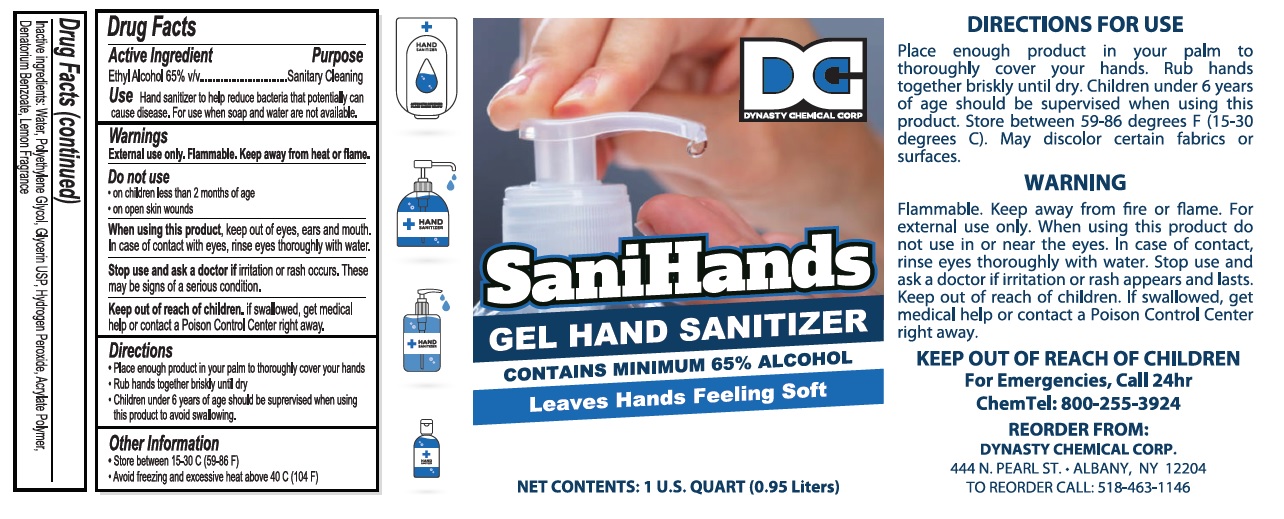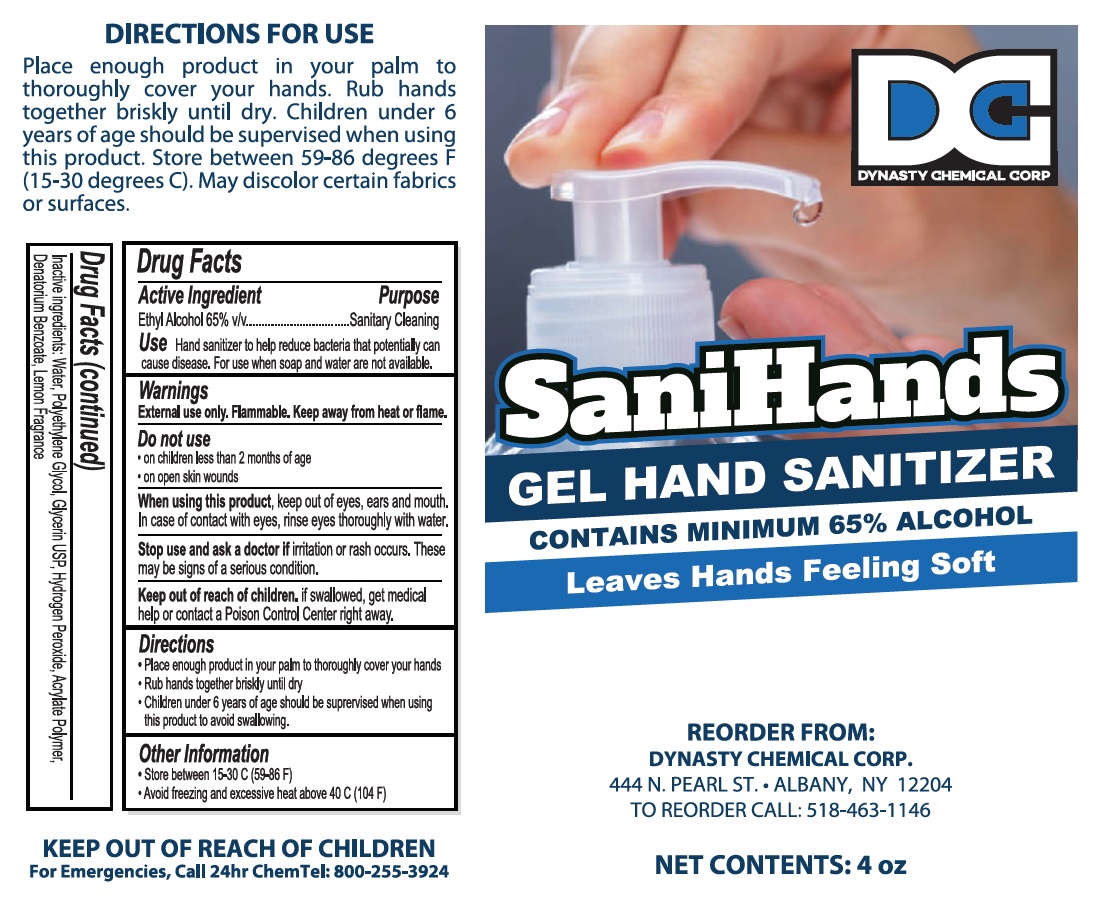 DRUG LABEL: SaniHands
NDC: 80497-001 | Form: GEL
Manufacturer: Dynasty Chemical Corp.
Category: otc | Type: HUMAN OTC DRUG LABEL
Date: 20201117

ACTIVE INGREDIENTS: ALCOHOL 65 mL/100 mL
INACTIVE INGREDIENTS: WATER; POLYETHYLENE GLYCOL, UNSPECIFIED; GLYCERIN; HYDROGEN PEROXIDE; DENATONIUM BENZOATE

SaniHands GEL HAND SANITIZER

Active Ingredient

Ethyl Alcohol 65% v/v

Purpose

Sanitary Cleaning

Use

Hand santizer to help reduce bacteria that potentially can cause disease. For use when soap and water are not available.

Warnings

External use only. Flammable. Keep away from heat or flame.

Do not use

• on children less than 2 months of age

• on open skin wounds

When using this product, keep out of eyes, ears and mouth. In case of contact with eyes, rinse eyes thoroughly with water.

Stop use and ask a doctor if irritation or rash occurs. These may be signs of a serious condition.

Keep out of reach of children. if swallowed, get medical help or contact a Poison Control Center right away.

Directions

• Place enough product in your palm to thoroughly cover your hands

• Rub hands together briskly until dry

• Children under 6 years of age should be supervised when using this product to avoid swallowing.

Other Information

• Store between 15-30 C (59-86 F)

• Avoid freezing and excessive heat above 40 C (104 F)

Inactive ingredients:

Water, Polyethylene Glycol, Glycerin USP, Hydrogen Peroxide, Acrylate Polymer, Denatorium Benzoate, Lemon Fragrance

CONTAINS MINIMUM 65% ALCOHOL

Leaves Hands Feeling Soft

DIRECTIONS FOR USE

Place enough product in your palm to thoroughly cover your hands. Rub hands together briskly until dry. Children under 6 years of age should be supervised when using this product. Store between 59-86 degrees F (15-30 degrees C). May discolor certain fabrics or surfaces.

KEEP OUT OF REACH OF CHILDREN

For Emergencies, Call 24hr ChemTel: 800-255-3924

REORDER FROM:

DYNASTY CHEMICAL CORP.

444 N.PEARL ST. • ALBANY, NY 12204

TO REORDER CALL: 518-463-1146